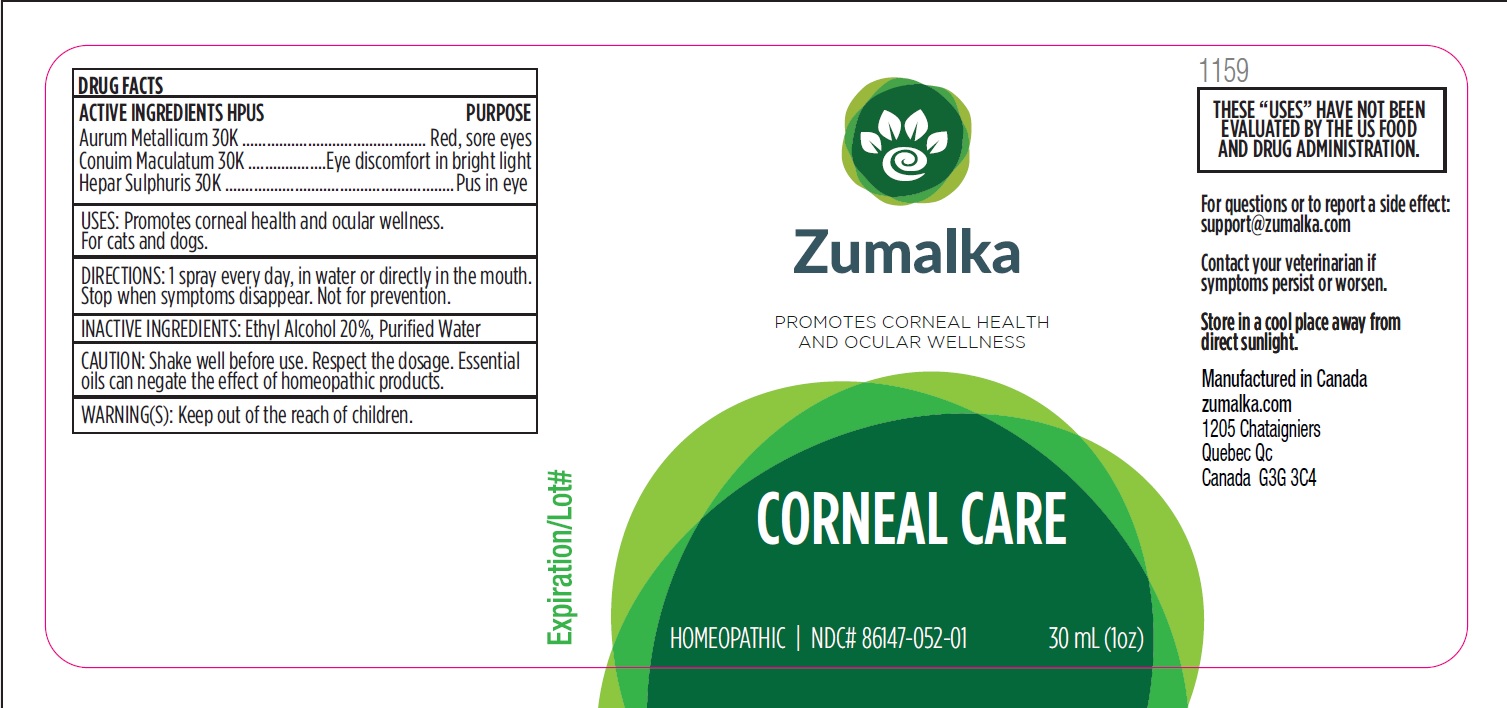 DRUG LABEL: CORNEAL CARE
NDC: 86147-052 | Form: LIQUID
Manufacturer: Groupe Cyrenne Inc.
Category: homeopathic | Type: OTC ANIMAL DRUG LABEL
Date: 20251120

ACTIVE INGREDIENTS: GOLD 30 [kp_C]/30 mL; CONIUM MACULATUM FLOWERING TOP 30 [kp_C]/30 mL; CALCIUM SULFIDE 30 [kp_C]/30 mL
INACTIVE INGREDIENTS: ALCOHOL; WATER

Active ingredients Purpose

Aurum Metallicum 30k Red, sore eyes

Conium Maculatum 30k Eye discomfort in bright light

Hepar Sulphuris 30k Pus in eye

Uses

Promotes corneal health and ocular wellness. For cats and dogs.

Warnings

Keep out of reach of children.

Direction

1 spray every day, in water or directly in the mouth. Stop when symptoms disappear. Not for prevention.

Inactive ingredients

Ethyl alcohol 20%, purified water

Cautions

Shake well before use. Respect the dosage. Essential oils can negate the effects of homeopathic products. Store in a cool place away from direct sunlight.